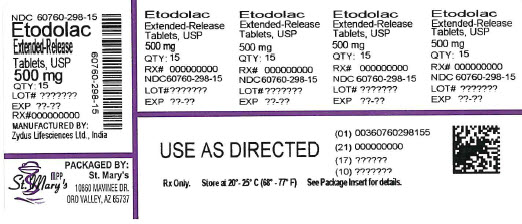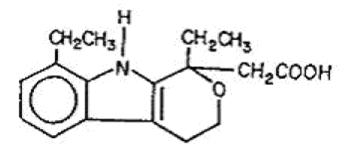 DRUG LABEL: Etodolac
NDC: 60760-298 | Form: TABLET, FILM COATED, EXTENDED RELEASE
Manufacturer: St. Mary's Medical Park Pharmacy
Category: prescription | Type: HUMAN PRESCRIPTION DRUG LABEL
Date: 20260121

ACTIVE INGREDIENTS: ETODOLAC 500 mg/1 1
INACTIVE INGREDIENTS: SODIUM PHOSPHATE, DIBASIC, ANHYDROUS; ETHYLCELLULOSE (100 MPA.S); FD&C BLUE NO. 2; FERROSOFERRIC OXIDE; FERRIC OXIDE YELLOW; HYPROMELLOSES; LACTOSE MONOHYDRATE; MAGNESIUM STEARATE; POLYETHYLENE GLYCOL, UNSPECIFIED; TALC; TITANIUM DIOXIDE; TRIACETIN

Etodolac Extended-release Tablets, USP

BOXED WARNING

Cardiovascular Thrombotic Events

WARNING: RISK OF SERIOUS CARDIOVASCULAR AND GASTROINTESTINAL EVENTS

Cardiovascular Thrombotic Events

Nonsteroidal anti-inflammatory drugs (NSAIDs) cause an increased risk of serious cardiovascular thrombotic events, including myocardial infarction and stroke, which can be fatal. This risk may occur early in treatment and may increase with duration of use [ see Warnings and Precautions ].

- Etodolac extended-release tablets are contraindicated in the setting of coronary artery bypass graft (CABG) surgery [ see Contraindications and Warnings and Precautions ] .

Gastrointestinal Bleeding, Ulceration, and Perforation

NSAIDs cause an increased risk of serious gastrointestinal (GI) adverse events including bleeding, ulceration, and perforation of the stomach or intestines, which can be fatal. These events can occur at any time during use and without warning symptoms. Elderly patients and patients with a prior history of peptic ulcer disease and/or GI bleeding are at greater risk for serious GI events [ see Warnings and Precautions].

DESCRIPTION

Etodolac extended-release tablets, USP contain etodolac, which is a member of the pyranocarboxylic acid group of non-steroidal anti-inflammatory drugs (NSAIDs). Each tablet contains etodolac for oral administration. Etodolac is a racemic mixture of [+]S and [-]R-enantiomers. Etodolac, USP is a white to off-white crystalline powder, insoluble in water but soluble in alcohols, chloroform, dimethyl sulfoxide, and aqueous polyethylene glycol.

The chemical name is (±) 1,8-diethyl-1,3,4,9-tetrahydropyrano-[3,4-b]indole-1-acetic acid. It has the following structural formula:

C17H21NO3 M.W. 287.36

Each etodolac extended-release tablet, USP intended for oral administration contains 400 mg or 500 mg or 600 mg of etodolac. In addition, each tablet contains the following inactive ingredients: disodium hydrogen phosphate, ethylcellulose, hypromellose, lactose monohydrate, magnesium stearate, polyethylene glycol, talc, titanium dioxide and triacetin. Additionally each 400 mg tablet contains: D&C yellow # 10 aluminum lake, FD&C Red # 40 aluminum lake and FD&C yellow # 6 aluminum lake and each 500 mg tablet contains: FD&C Blue # 2 aluminum lake, iron oxide black and iron oxide yellow and each 600 mg tablet contains: FD&C blue # 2 aluminum lake, iron oxide red and iron oxide yellow.

The USP Drug Release test complies with USP Dissolution Test 1.

CLINICAL PHARMACOLOGY

Pharmacodynamics

Etodolac extended-release tablets are a non-steroidal anti-inflammatory drug (NSAID) that exhibits anti-inflammatory, analgesic, and antipyretic activities in animal models. The mechanism of action of etodolac extended-release tablets, like that of other NSAIDs, is not completely understood, but may be related to prostaglandin synthetase inhibition.

Pharmacokinetics

Absorption

Etodolac extended-release tablets and etodolac tablets both contain etodolac, but differ in their release characteristics. The systemic availability of etodolac from etodolac extended-release tablets is generally greater than 80%. Etodolac does not undergo significant first-pass metabolism following oral administration. After oral administration of etodolac extended-release tablets in doses up to 800 mg once daily, peak concentrations occur approximately 6 hours after dosing and are dose proportional for both total and free etodolac.

Table 1 shows the comparison of etodolac pharmacokinetic parameters after the administration of etodolac tablets and etodolac extended-release tablets.

Table 2 shows the etodolac pharmacokinetic parameters in various populations. The data from patients with renal and hepatic impairment were obtained following administration of (immediate-release) etodolac tablets.

Table 1
 | Mean (CV)% [% Coefficient of variation]
Pharmacokinetic Parameters | Etodolac Tablets | Etodolac Extended-release Tablets
Extent of Oral Absorption (Bioavailability) [F] | ≥ 80% | ≥ 80%
Time to Peak Concentration (Tmax), h | 1.4 (61%) | 6.7 (47%)
Oral Clearance (CL/F), mL/h/kg | 49.1 (33%) | 46.8 (37%)
Apparent Volume of Distribution (Vd/F), mL/kg | 393 (29%) | 566 (26%)
Terminal Half-Life (t1/2), h | 6.4 (22%) | 8.4 (30%)

Table 2 Mean (CV%)* Pharmacokinetic Parameters of Etodolac in Normal Healthy Adults and Various Special Populations
 | Etodolac Extended-release Tablets |  |  |  | Etodolac Tablets
PK Parameters | Normal Healthy Adults | Healthy Males | Healthy Females | Elderly (> 65 yr) | Hemodialysis† (24 to 65) (n = 9) |  | Renal Impairment† | Hepatic Impairment†
 | (18 to 44)‡ (n = 116) | (18 to 43) (n = 102) | (25 to 44) (n = 14) | (66 to 88) (n = 24) | Dialysis On | Dialysis Off | (46 to 73) (n = 10) | (34 to 60) (n = 9)
Tmax, h | 6.7 (47%)* | 6.8 (45%) | 4.5 (56%) | 6.2 (51%) | 1.7 (88%) | 0.9 (67%) | 2.1 (46%) | 1.1 (15%)
Oral Clearance, mL/h/kg (CL/F) | 46.8 (37%) | 46.8 (37%) | 47.2 (38%) | 51.6 (40%) | NA | NA | 58.3 (19%) | 42 (43%)
Apparent Volume of Distribution, mL/kg (Vd/F) | 566 (26%) | 580 (26%) | 459 (28%) | 552 (34%) | NA | NA | NA | NA
Terminal Half- Life, h | 8.4 (30%) | 8.4 (29%) | 7.6 (45%) | 7.8 (26%) | 5.1 (22%) | 7.5 (34%) | NA | 5.7 (24%)
* % Coefficient of variation
† Pharmacokinetic parameters obtained following administration of etodolac tablets
‡ Age range (years)
NA = not available

Food/Antacid Effects

Food has no significant effect on the extent of etodolac extended-release tablets absorption, however, food significantly increased Cmax (54%) following a 600 mg dose.

The extent of absorption of etodolac is not affected when etodolac is administered with antacid. Coadministration, with an antacid, decreases the peak concentration reached by about 15 to 20% with no measurable effect on time-to-peak.

Distribution

The mean apparent volume of distribution (Vd/F) of etodolac following administration of etodolac extended-release tablets is 566 mL/kg. Etodolac is more than 99% bound to plasma proteins, primarily to albumin, and is independent of etodolac concentration over the dose range studied. It is not known whether etodolac is excreted in human milk. However, based on its physical-chemical properties, excretion into breast milk is expected.

Metabolism

Etodolac metabolites do not contribute significantly to the pharmacological activity of etodolac extended-release tablets.

Following administration of immediate-release etodolac, several metabolites have been identified in human plasma and urine. Other metabolites remain to be identified. The metabolites include 6-, 7-, and 8-hydroxylated etodolac and etodolac glucuronide. After a single dose of^14C-etodolac, hydroxylated metabolites accounted for less than 10% of total drug in serum. On chronic dosing, hydroxylated-etodolac metabolites do not accumulate in the plasma of patients with normal renal function. The extent of accumulation of hydroxylated-etodolac metabolites in patients with renal dysfunction has not been studied. The role, if any, of a specific cytochrome P450 system in the metabolism of etodolac is unknown. The hydroxylated-etodolac metabolites undergo further glucuronidation followed by renal excretion and partial elimination in the feces.

Excretion

The mean oral clearance of etodolac following oral etodolac extended-release tablets dosing is 47 (±17) mL/h/kg. The terminal half-life (t1/2) of etodolac after etodolac extended-release tablets administration is 8.4 hours compared to 6.4 hours for etodolac tablets. Approximately 1% of an etodolac tablet dose is excreted unchanged in the urine, with 72% of the dose excreted into the urine as parent drug plus metabolites:

- etodolac, unchanged | 1%
- etodolac glucuronide | 13%
- hydroxylated metabolites (6-, 7-, and 8-OH) | 5%
- hydroxylated metabolite glucuronides | 20%
- unidentified metabolites | 33%

Fecal excretion accounted for 16% of the dose.

Geriatric

In clinical studies, age was not shown to have any effect on half-life or protein binding, and demonstrated no change in expected drug accumulation. No dosage adjustment is generally necessary in the elderly on the basis of pharmacokinetics. The elderly may need dosage adjustment, however, as they may be more sensitive to antiprostaglandin effects than younger patients (see PRECAUTIONS, Geriatric Use).

Pediatric

The pharmacokinetics of etodolac extended-release tablets were assessed in an open-label, 12 week clinical trial which included plasma sampling for population pharmacokinetics. Seventy-two (72) patients, 6 to 16 years of age, with juvenile rheumatoid arthritis, received etodolac extended-release tablets in doses of 13.3 to 21.3 mg/kg given as 400 to 1000 mg once daily. The results from a population pharmacokinetic analysis based on the 59 subjects who completed the trial are as follows:

Table 3 Pharmacokinetic Parameter Estimates for Etodolac Extended-release Tablets in Patients with Juvenile Rheumatoid Arthritis
Parameter | JRA [Mean (CV) of parameter estimates predicted from population pharmacokinetics] (Age:6 to 16) [Age range (years)] n = 59
Oral Clearance (CL/F), mL/h/kg | 47.8 (38%)
Apparent Volume of Distribution (Vd/F), mL/kg | 78.9 (61%)
Half-life (t1/2), h | 12.1 (75%)

While similar, the pharmacokinetic parameters for children with juvenile rheumatoid arthritis did not directly correlate with adult pharmacokinetic data in rheumatoid arthritis. In the population pharmacokinetic analysis, body weights below 50 kg were found to correlate with CL/F (see DOSAGE AND ADMINISTRATION).

Race

Pharmacokinetic differences due to race have not been identified. Clinical studies included patients of many races, all of whom responded in a similar fashion.

Hepatic Insufficiency

The pharmacokinetics of etodolac following administration of etodolac extended-release tablets have not been investigated in subjects with hepatic insufficiency. Following administration of etodolac tablets, the plasma protein binding and disposition of total and free etodolac were unchanged in the presence of compensated hepatic cirrhosis. Although no dosage adjustment is generally required in patients with chronic hepatic diseases, etodolac clearance is dependent on liver function and could be reduced in patients with severe hepatic failure.

Renal Insufficiency

The pharmacokinetics of etodolac following administration of etodolac extended-release tablets have not been investigated in subjects with renal insufficiency. Etodolac renal clearance following administration of etodolac tablets was unchanged in the presence of mild-to-moderate renal failure (creatinine clearance, 37 to 88 mL/min). Although renal elimination is a significant pathway of excretion for etodolac metabolites, no dosing adjustment in patients with mild to moderate renal dysfunction is generally necessary. Etodolac plasma protein binding decreases in patients with severe renal deficiency. Etodolac should be used with caution in such patients because, as with other NSAIDs, it may further decrease renal function in some patients. Etodolac is not significantly removed from the blood in patients undergoing hemodialysis.

CLINICAL STUDIES

Arthritis

The use of etodolac extended-release tablets in managing the signs and symptoms of osteoarthritis of the knee and rheumatoid arthritis was assessed in doubleblind, randomized, parallel, controlled clinical trials in 1552 patients. In these trials, etodolac extended-release tablets, given once daily, provided efficacy comparable to immediate-release etodolac.

The safety, efficacy, and pharmacokinetics of etodolac extended-release tablets were assessed in an open-label, 12 week clinical trial. Seventy-two (72) patients, 6 to 16 years of age, with juvenile rheumatoid arthritis, received etodolac extended-release tablets in doses of 400 to 1000 mg (13.3 to 21.3 mg/kg body weight) once daily. At these doses, etodolac extended-release tablets controlled the signs and symptoms of juvenile rheumatoid arthritis. Based on the results of this study, the safety profile of etodolac extended-release tablets (at doses not exceeding 20 mg/kg) appeared to be similar to that observed in the adult arthritic patients in clinical trials (see PRECAUTIONS, Pediatric Use).

INDICATIONS AND USAGE

Carefully consider the potential benefits and risks of etodolac extended-release tablets, USP and other treatment options before deciding to use etodolac extended-release tablets, USP. Use the lowest effective dose for the shortest duration consistent with individual patient treatment goals (see WARNINGS).

Etodolac extended-release tablets, USP are indicated:

* For relief of signs and symptoms of juvenile arthritis

* For relief of the signs and symptoms of rheumatoid arthritis

* For relief of the signs and symptoms of osteoarthritis

CONTRAINDICATIONS

Etodolac extended-release tablets are contraindicated in patients with known hypersensitivity to etodolac.

Etodolac extended-release tablets should not be given to patients who have experienced asthma, urticaria, or allergic-type reactions after taking aspirin or other NSAIDs. Severe, rarely fatal, anaphylactic-like reactions to NSAIDs have been reported in such patients (see WARNINGS, Anaphylactoid Reactions and PRECAUTIONS, Preexisting Asthma).

Etodolac extended-release tablets are contraindicated in the setting of coronary artery bypass graft (CABG) surgery (see WARNINGS).

WARNINGS

Cardiovascular Thrombotic Events

Clinical trials of several COX-2 selective and nonselective NSAIDs of up to three years duration have shown an increased risk of serious cardiovascular (CV) thrombotic events, including myocardial infarction (MI) and stroke, which can be fatal. Based on available data, it is unclear that the risk for CV thrombotic events is similar for all NSAIDs. The relative increase in serious CV thrombotic events over baseline conferred by NSAID use appears to be similar in those with and without known CV disease or risk factors for CV disease. However, patients with known CV disease or risk factors had a higher absolute incidence of excess serious CV thrombotic events, due to their increased baseline rate. Some observational studies found that this increased risk of serious CV thrombotic events began as early as the first weeks of treatment. The increase in CV thrombotic risk has been observed most consistently at higher doses.

To minimize the potential risk for an adverse CV event in NSAID-treated patients, use the lowest effective dose for the shortest duration possible. Physicians and patients should remain alert for the development of such events, throughout the entire treatment course, even in the absence of previous CV symptoms. Patients should be informed about the symptoms of serious CV events and the steps to take if they occur.

There is no consistent evidence that concurrent use of aspirin mitigates the increased risk of serious CV thrombotic events associated with NSAID use. The concurrent use of aspirin and an NSAID, such as etodolac, increases the risk of serious gastrointestinal (GI) events [ see Warnings].

Status Post Coronary Artery Bypass Graft (CABG) Surgery

Two large, controlled clinical trials of a COX-2 selective NSAID for the treatment of pain in the first 10–14 days following CABG surgery found an increased incidence of myocardial infarction and stroke. NSAIDs are contraindicated in the setting of CABG [ see Contraindications].

Post-MI Patients

Observational studies conducted in the Danish National Registry have demonstrated that patients treated with NSAIDs in the post-MI period were at increased risk of reinfarction, CV-related death, and all-cause mortality beginning in the first week of treatment. In this same cohort, the incidence of death in the first year post MI was 20 per 100 person years in NSAID-treated patients compared to 12 per 100 person years in non-NSAID exposed patients. Although the absolute rate of death declined somewhat after the first year post-MI, the increased relative risk of death in NSAID users persisted over at least the next four years of follow-up.

Avoid the use of etodolac extended-release tablets in patients with a recent MI unless the benefits are expected to outweigh the risk of recurrent CV thrombotic events. If etodolac extended-release tablets are used in patients with a recent MI, monitor patients for signs of cardiac ischemia.

Hypertension

NSAIDs, including etodolac extended-release tablets, can lead to onset of new hypertension or worsening of preexisting hypertension, either of which may contribute to the increased incidence of CV events. Patients taking thiazides or loop diuretics may have impaired response to these therapies when taking NSAIDs. NSAIDs, including etodolac extended-release tablets, should be used with caution in patients with hypertension. Blood pressure (BP) should be monitored closely during the initiation of NSAID treatment and throughout the course of therapy.

Heart Failure and Edema

The Coxib and traditional NSAID Trialists' Collaboration meta-analysis of randomized

controlled trials demonstrated an approximately two-fold increase in hospitalizations for heart failure in COX-2 selective-treated patients and nonselective NSAID-treated patients compared to placebo-treated patients. In a Danish National Registry study of patients with heart failure, NSAID use increased the risk of MI, hospitalization for heart failure, and death.

Additionally, fluid retention and edema have been observed in some patients treated with NSAIDs. Use of etodolac may blunt the CV effects of several therapeutic agents used to treat these medical conditions [e.g., diuretics, ACE inhibitors, or angiotensin receptor blockers (ARBs)] [see Drug Interactions].

Avoid the use of etodolac extended-release tablets in patients with severe heart failure unless the benefits are expected to outweigh the risk of worsening heart failure. If etodolac extended-release tablets are used in patients with severe heart failure, monitor patients for signs of worsening heart failure.

Gastrointestinal Effects - Risk of Ulceration, Bleeding, and Perforation

NSAIDs, including etodolac extended-release tablets, can cause serious gastrointestinal (GI) adverse events including inflammation, bleeding, ulceration, and perforation of the stomach, small intestine, or large intestine, which can be fatal. These serious adverse events can occur at any time, with or without warning symptoms, in patients treated with NSAIDs. Only one in five patients, who develop a serious upper GI adverse event on NSAID therapy, is symptomatic. Upper GI ulcers, gross bleeding, or perforation caused by NSAIDs occur in approximately 1% of patients treated for 3 to 6 months, and in about 2 to 4% of patients treated for one year. These trends continue with longer duration of use, increasing the likelihood of developing a serious GI event at some time during the course of therapy. However, even short-term therapy is not without risk.

NSAIDs should be prescribed with extreme caution in those with a prior history of ulcer disease or gastrointestinal bleeding. Patients with a prior history of peptic ulcer disease and/or gastrointestinal bleeding who use NSAIDs have a greater than 10 fold increased risk for developing a GI bleed compared to patients with neither of these risk factors. Other factors that increase the risk for GI bleeding in patients treated with NSAIDs include concomitant use of oral corticosteroids or anticoagulants, longer duration of NSAID therapy, smoking, use of alcohol, older age, and poor general health status. Most spontaneous reports of fatal GI events are in elderly or debilitated patients and therefore, special care should be taken in treating this population.

To minimize the potential risk for an adverse GI event in patients treated with an NSAID, the lowest effective dose should be used for the shortest possible duration. Patients and physicians should remain alert for signs and symptoms of GI ulceration and bleeding during NSAID therapy and promptly initiate additional evaluation and treatment if a serious GI adverse event is suspected. This should include discontinuation of the NSAID until a serious GI adverse event is ruled out. For high risk patients, alternate therapies that do not involve NSAIDs should be considered.

Renal Effects

Long-term administration of NSAIDs has resulted in renal papillary necrosis and other renal injury. Renal toxicity has also been seen in patients in whom renal prostaglandins have a compensatory role in the maintenance of renal perfusion. In these patients, administration of a nonsteroidal anti-inflammatory drug may cause a dose-dependent reduction in prostaglandin formation and, secondarily, in renal blood flow, which may precipitate overt renal decompensation. Patients at greatest risk of this reaction are those with impaired renal function, heart failure, liver dysfunction, those taking diuretics and ACE inhibitors, and the elderly. Discontinuation of NSAID therapy is usually followed by recovery to the pretreatment state.

Advanced Renal Disease

No information is available from controlled clinical studies regarding the use of etodolac extended-release tablets in patients with advanced renal disease. Therefore, treatment with etodolac extended-release tablets is not recommended in these patients with advanced renal disease. If etodolac extended-release tablet therapy must be initiated, close monitoring of the patient’s renal function is advisable.

Anaphylactoid Reactions

As with other NSAIDs, anaphylactoid reactions may occur in patients without known prior exposure to etodolac extended-release tablets. Etodolac extended-release tablets should not be given to patients with the aspirin triad. This symptom complex typically occurs in asthmatic patients who experience rhinitis with or without nasal polyps, or who exhibit severe, potentially fatal bronchospasm after taking aspirin or other NSAIDs (see CONTRAINDICATIONS and PRECAUTIONS, Preexisting Asthma). Emergency help should be sought in cases where an anaphylactoid reaction occurs.

Skin Reactions

NSAIDs, including etodolac extended-release tablets, can cause serious skin adverse events such as exfoliative dermatitis, Stevens-Johnson Syndrome (SJS), and toxic epidermal necrolysis (TEN), which can be fatal. These serious events may occur without warning. Patients should be informed about the signs and symptoms of serious skin manifestations and use of the drug should be discontinued at the first appearance of skin rash or any other sign of hypersensitivity.

Pregnancy

In late pregnancy, as with other NSAIDs, etodolac extended-release tablets should be avoided because it may cause premature closure of the ductus arteriosus.

PRECAUTIONS

General

Etodolac extended-release tablets cannot be expected to substitute for corticosteroids or to treat corticosteroid insufficiency. Abrupt discontinuation of corticosteroids may lead to disease exacerbation. Patients on prolonged corticosteroid therapy should have their therapy tapered slowly if a decision is made to discontinue corticosteroids.

The pharmacological activity of etodolac extended-release tablets in reducing fever and inflammation may diminish the utility of these diagnostic signs in detecting complications of presumed noninfectious, painful conditions.

Hepatic Effects

Borderline elevations of one or more liver tests may occur in up to 15% of patients taking NSAIDs including etodolac extended-release tablets. These laboratory abnormalities may progress, may remain unchanged, or may be transient with continuing therapy. Notable elevations of ALT or AST (approximately three or more times the upper limit of normal) have been reported in approximately 1% of patients in clinical trials with NSAIDs. In addition, rare cases of severe hepatic reactions, including jaundice and fatal fulminant hepatitis, liver necrosis and hepatic failure, some of them with fatal outcomes have been reported.

A patient with symptoms and/or signs suggesting liver dysfunction, or in whom an abnormal liver test has occurred, should be evaluated for evidence of the development of a more severe hepatic reaction while on therapy with etodolac extended-release tablets. If clinical signs and symptoms consistent with liver disease develop, or if systemic manifestations occur (e.g., eosinophilia, rash, etc.), etodolac extended-release tablets should be discontinued.

Hematological Effects

Anemia is sometimes seen in patients receiving NSAIDs, including etodolac extended-release tablets. This may be due to fluid retention, occult or gross GI blood loss, or an incompletely described effect upon erythropoiesis. Patients on long-term treatment with NSAIDs, including etodolac extended-release tablets, should have their hemoglobin or hematocrit checked if they exhibit any signs or symptoms of anemia.

NSAIDs inhibit platelet aggregation and have been shown to prolong bleeding time in some patients. Unlike aspirin, their effect on platelet function is quantitatively less, of shorter duration, and reversible. Patients receiving etodolac extended-release tablets who may be adversely affected by alterations in platelet function, such as those with coagulation disorders or patients receiving anticoagulants, should be carefully monitored.

Preexisting Asthma

Patients with asthma may have aspirin-sensitive asthma. The use of aspirin in patients with aspirin-sensitive asthma has been associated with severe bronchospasm which can be fatal. Since cross reactivity, including bronchospasm, between aspirin and other nonsteroidal anti-inflammatory drugs has been reported in such aspirin-sensitive patients, etodolac extended-release tablets should not be administered to patients with this form of aspirin sensitivity and should be used with caution in patients with preexisting asthma.

Information for Patients

Patients should be informed of the following information before initiating therapy with an NSAID and periodically during the course of ongoing therapy. Patients should also be encouraged to read the NSAID Medication Guide that accompanies each prescription dispensed.

1. Cardiovascular Thrombotic Events: Advise patients to be alert for the symptoms of cardiovascular thrombotic events, including chest pain, shortness of breath, weakness, or slurring of speech, and to report any of these symptoms to their health care provider immediately [ see Warnings].
2. Etodolac extended-release tablets, like other NSAIDs, can cause GI discomfort and, rarely, serious GI side effects, such as ulcers and bleeding, which may result in hospitalization and even death. Although serious GI tract ulcerations and bleeding can occur without warning symptoms, patients should be alert for the signs and symptoms of ulcerations and bleeding, and should ask for medical advice when observing any indicative sign or symptoms including epigastric pain, dyspepsia, melena, and hematemesis. Patients should be apprised of the importance of this follow-up (see WARNINGS, Gastrointestinal Effects - Risk of Ulceration, Bleeding, and Perforation).
3. Etodolac extended-release tablets, like other NSAIDs, can cause serious skin side effects such as exfoliative dermatitis, SJS, and TEN, which may result in hospitalizations and even death. Although serious skin reactions may occur without warning, patients should be alert for the signs and symptoms of skin rash and blisters, fever, or other signs of hypersensitivity such as itching, and should ask for medical advice when observing any indicative signs or symptoms. Patients should be advised to stop the drug immediately if they develop any type of rash and contact their physicians as soon as possible.
4. Heart Failure And Edema: Advise patients to be alert for the symptoms of congestive heart failure including shortness of breath, unexplained weight gain, or edema and to contact their healthcare provider if such symptoms occur [ see Warnings].
5. Patients should be informed of the warning signs and symptoms of hepatotoxicity (e.g., nausea, fatigue, lethargy, pruritus, jaundice, right upper quadrant tenderness, and "flu-like" symptoms). If these occur, patients should be instructed to stop therapy and seek immediate medical therapy.
6. Patients should be informed of the signs of an anaphylactoid reaction (e.g., difficulty breathing, swelling of the face or throat). If these occur, patients should be instructed to seek immediate emergency help (see WARNINGS).
7. In late pregnancy, as with other NSAIDs, etodolac extended-release tablets should be avoided because it will cause premature closure of the ductus arteriosus.

Laboratory Tests

Because serious GI tract ulcerations and bleeding can occur without warning symptoms, physicians should monitor for signs or symptoms of GI bleeding. Patients on long-term treatment with NSAIDs, should have their CBC and a chemistry profile checked periodically. If clinical signs and symptoms consistent with liver or renal disease develop, systemic manifestations occur (e.g., eosinophilia, rash, etc.) or if abnormal liver tests persist or worsen, etodolac extended-release tablets should be discontinued.

ACE-inhibitors

Reports suggest that NSAIDs may diminish the antihypertensive effect of ACE-inhibitors. This interaction should be given consideration in patients taking NSAIDs concomitantly with ACE-inhibitors.

Aspirin

When etodolac extended-release tablets are administered with aspirin, its protein binding is reduced, although the clearance of free etodolac is not altered. The clinical significance of this interaction is not known; however, as with other NSAIDs, concomitant administration of etodolac extended-release tablets and aspirin is not generally recommended because of the potential of increased adverse effects.

Cyclosporine and Digoxin

Etodolac extended-release tablets, like other NSAIDs, through effects on renal prostaglandins, may cause changes in the elimination of these drugs, leading to elevated serum levels of cyclosporine and digoxin and increased toxicity. Nephrotoxicity associated with cyclosporine may also be enhanced. Patients receiving these drugs who are given etodolac extended-release tablets, or any other NSAID, and particularly those patients with altered renal function, should be observed for the development of the specific toxicities of these drugs.

Furosemide

Clinical studies, as well as post marketing observations, have shown that etodolac extended-release tablets can reduce the natriuretic effect of furosemide and thiazides in some patients. This response has been attributed to inhibition of renal prostaglandin synthesis. During concomitant therapy with NSAIDs, the patient should be observed closely for signs of renal failure (see WARNINGS, Renal Effects), as well as to assure diuretic efficacy.

Lithium

NSAIDs have produced an elevation of plasma lithium levels and a reduction in renal lithium clearance. The mean minimum lithium concentration increased 15% and the renal clearance was decreased by approximately 20%. These effects have been attributed to inhibition of renal prostaglandin synthesis by the NSAID. Thus, when NSAIDs and lithium are administered concurrently, subjects should be observed carefully for signs of lithium toxicity.

Methotrexate

NSAIDs have been reported to competitively inhibit methotrexate accumulation in rabbit kidney slices. This may indicate that they could enhance the toxicity of methotrexate. Caution should be used when NSAIDs are administered concomitantly with methotrexate.

Phenylbutazone

Phenylbutazone causes an increase (by about 80%) in the free fraction of etodolac. Although in vivo studies have not been done to see if etodolac clearance is changed by coadministration of phenylbutazone, it is not recommended that they be coadministered.

Warfarin

The effects of warfarin and NSAIDs on GI bleeding are synergistic, such that users of both drugs together have a risk of serious GI bleeding higher than users of either drug alone.

Drug/Laboratory Test Interactions

The urine of patients who take etodolac can give a false-positive reaction for urinary bilirubin (urobilin) due to the presence of phenolic metabolites of etodolac. Diagnostic dip-stick methodology, used to detect ketone bodies in urine, has resulted in false-positive findings in some patients treated with etodolac. Generally, this phenomenon has not been associated with other clinically significant events. No dose relationship has been observed.

Etodolac treatment is associated with a small decrease in serum uric acid levels. In clinical trials, mean decreases of 1 to 2 mg/dL were observed in arthritic patients receiving etodolac (600 mg to 1000 mg/day) after 4 weeks of therapy. These levels then remained stable for up to 1 year of therapy.

Carcinogenesis, Mutagenesis, Impairment of Fertility

No carcinogenic effect of etodolac was observed in mice or rats receiving oral doses of 15 mg/kg/day (45 to 89 mg/m^2, respectively) or less for periods of 18 months or 2 years, respectively. Etodolac was not mutagenic in in vitro tests performed with S. typhimurium and mouse lymphoma cells as well as in an in vivo mouse micronucleus test. However, data from the in vitro human peripheral lymphocyte test showed an increase in the number of gaps (3% to 5% unstained regions in the chromatid without dislocation) among the etodolac-treated cultures (50 to 200 g/mL) compared to negative controls (2%); no other difference was noted between the controls and drug-treated groups. Etodolac showed no impairment of fertility in male and female rats up to oral doses of 16 mg/kg (94 mg/m^2). However, reduced implantation of fertilized eggs occurred in the 8 mg/kg group.

Teratogenic Effects

Pregnancy category C

Reproductive studies conducted in rats and rabbits have not demonstrated evidence of developmental abnormalities. However, animal reproduction studies are not always predictive of human response. There are no adequate and well-controlled studies in pregnant women.

Nonteratogenic Effects

Because of the known effects of nonsteroidal anti-inflammatory drugs on the fetal cardiovascular system (closure of ductus arteriosus), use during pregnancy (particularly late pregnancy) should be avoided.

Labor and Delivery

In rat studies with NSAIDs, as with other drugs known to inhibit prostaglandin synthesis, an increased incidence of dystocia, delayed parturition, and decreased pup survival occurred. The effects of etodolac extended-release tablets on labor and delivery in pregnant women are unknown.

Nursing Mothers

It is not known whether this drug is excreted in human milk. Because many drugs are excreted in human milk and because of the potential for serious adverse reactions in nursing infants from etodolac extended-release tablets, a decision should be made whether to discontinue nursing or to discontinue the drug, taking into account the importance of the drug to the mother.

Pediatric Use

Safety and effectiveness in pediatric patients below the age of 6 years have not been established.

Geriatric Use

As with any NSAIDs, caution should be exercised in treating the elderly (65 years and older).

ADVERSE REACTIONS

A total of 1552 patients were exposed to etodolac extended-release tablets in controlled clinical studies of at least 4 weeks in length and using daily doses in the range of 400 to 1200 mg. In the tabulations below, adverse event rates are generally categorized based on the incidence of events in the first 30 days of treatment with etodolac extended-release tablets. As with other NSAIDs, the cumulative adverse event rates may increase significantly over time with extended therapy.

In patients taking NSAIDs, including etodolac extended-release tablets, the most frequently reported adverse experiences occurring in approximately 1 to 10% of patients are:

Gastrointestinal experiences including

abdominal pain | constipation | Diarrhea
dyspepsia | flatulence | GI ulcers (gastric/duodenal)*
gross bleeding/perforation* | nausea | Vomiting

Other events including:

abnormal renal function [Adverse events that were observed in < 1% of patients in the first 30 days of treatment with etodolac extended-release tablets in clinical trials.] | Anemia | asthenia
dizziness | edema | elevated liver enzymes
headaches | hypertension | increased bleeding time
infection | pharyngitis | pruritus
rashes | rhinitis | tinnitus

Body as a whole

Allergic reaction, anaphylactic/anaphylactoid reactions (including shock), chills, fever, sepsis

Cardiovascular system

Congestive heart failure, flushing, palpitations, tachycardia, syncope, vasculitis (including necrotizing and allergic)

Digestive system

Anorexia, cholestatic hepatitis, cholestatic jaundice, dry mouth, duodenitis, eructation, esophagitis, gastritis, gastric/peptic ulcers, glossitis, hepatic failure, hepatitis, hematemesis, intestinal ulceration, jaundice, liver necrosis, melena, pancreatitis, rectal bleeding, stomatitis

Hemic and lymphatic system

Agranulocytosis, ecchymosis, eosinophilia, hemolytic anemia, leukopenia, neutropenia, pancytopenia, purpura, thrombocytopenia

Metabolic and nutritional

Hyperglycemia in previously controlled diabetic patients

Nervous system

Anxiety, confusion, depression, dream abnormalities, insomnia, nervousness, paresthesia, somnolence, tremors, vertigo

Respiratory system

Asthma, dyspnea, pulmonary infiltration with eosinophilia

Skin and appendages

Angioedema, cutaneous vasculitis with purpura, erythema multiforme, hyperpigmentation, sweating, urticaria, vesiculobullous rash

Special senses

Blurred vision, photophobia, transient visual disturbances

Urogenital system

Dysuria, elevated BUN, oliguria/polyuria, proteinuria, renal failure, renal insufficiency, renal papillary necrosis, serum creatinine increase, urinary frequency

Other NSAID Adverse Reactions, Which Occur Rarely Are

Body as a whole

Anaphylactic reactions, appetite changes, death

Cardiovascular system

Arrhythmia, cerebrovascular accident, hypotension, myocardial infarction

Digestive system

Colitis, esophagitis with or without stricture or cardiospasm, thirst, ulcerative stomatitis

Hemic and lymphatic system

Aplastic anemia, lymphadenopathy

Metabolic and nutritional

Change in weight

Nervous system

Coma, convulsions, hallucinations, meningitis

Respiratory

Bronchitis, pneumonia, respiratory depression, sinusitis

Skin and appendages

Alopecia, exfoliative dermatitis, maculopapular rash, photosensitivity, skin peeling, Stevens-Johnson syndrome, toxic epidermal necrosis

Special senses

Conjunctivitis, deafness, hearing impairment, taste perversion

Urogenital system

Cystitis, hematuria, interstitial nephritis, leukorrhea, renal calculus, uterine bleeding irregularities

OVERDOSAGE

Symptoms following acute NSAID overdose are usually limited to lethargy, drowsiness, nausea, vomiting, and epigastric pain, which are generally reversible with supportive care. Gastrointestinal bleeding can occur. Hypertension, acute renal failure, respiratory depression and coma may occur, but are rare. Anaphylactoid reactions have been reported with therapeutic ingestion of NSAIDs, and may occur following an overdose.

Patients should be managed by symptomatic and supportive care following an NSAID overdose. There are no specific antidotes.

Emesis and/or activated charcoal (60 to 100 g in adults, 1 to 2 g/kg in children) and/or osmotic cathartic may be indicated in patients seen within 4 hours of ingestion with symptoms or following a large overdose (5 to 10 times the usual dose). Forced diuresis, alkalinization of the urine, hemodialysis, or hemoperfusion may not be useful due to high protein binding.

DOSAGE AND ADMINISTRATION

Carefully consider the potential benefits and risks of etodolac extended-release tablets and other treatment options before deciding to use etodolac extended-release tablets. Use the lowest effective dose for the shortest duration consistent with individual patient treatment goals (see WARNINGS).

After observing the response to initial therapy with etodolac extended-release tablets, the dose and frequency should be adjusted to suit an individual patient’s needs.

Juvenile Rheumatoid Arthritis

For the relief of the signs and symptoms of juvenile rheumatoid arthritis in patients 6 to 16 years of age, the recommended dose given orally once per day should be based on body weight, according to the following table:

Table 4
Body Weight Range (kg) | Dose
20 to 30 | 400 mg Tablet x 1
31 to 45 | 600 mg Tablet x 1
46 to 60 | 400 mg Tablet x 2
> 60 | 500 mg Tablet x 2

Rheumatoid Arthritis and Osteoarthritis

For the relief of the signs and symptoms of osteoarthritis or rheumatoid arthritis, the recommended starting dose of etodolac extended-release tablets is 400 to 1000 mg given orally once per day.

As with other NSAIDs, the lowest effective dose should be sought for each patient. In chronic conditions, a therapeutic response to therapy with etodolac extended-release tablets is sometimes seen within one week of therapy, but most often is observed by two weeks.

HOW SUPPLIED

Etodolac Extended-release Tablets USP, 500 mg are grey-colored, oval-shaped, beveled edged, film-coated tablets, debossed with "272" on one side and plain on other side and are supplied as follows:

NDC 60760-298-15 BOTTLES OF 15

Storage:

Store at 20° to 25°C (68° to 77°F) [See USP Controlled Room Temperature].

Protect from excessive heat and humidity.

Dispense in a tight, light-resistant container with a child-resistant closure.

Manufactured by:

Cadila Healthcare Ltd.

Ahmedabad, India

Distributed by:

Zydus Pharmaceuticals USA Inc.

Pennington, NJ 08534

Rev.: 06/16

Medication Guide

For Nonsteroidal Anti-inflammatory Drugs (NSAIDs)

Etodolac

(e-TOE-doe-lak)

Extended-release Tablets, USP

What is the most important information I should know about medicines called Nonsteroidal Anti- inflammatory Drugs (NSAIDs)?

NSAIDs can cause serious side effects, including:

- Increased risk of a heart attack or stroke that can lead to death . This risk may happen early in treatment and may increase:

○ with increasing doses of NSAIDs

○ with longer use of NSAIDs

Do not take NSAIDs right before or after a heart surgery called a "coronary artery bypass graft (CABG)." Avoid taking NSAIDs after a recent heart attack, unless your healthcare provider tells you to. You may have an increased risk of another heart attack if you take NSAIDs after a recent heart attack.

- Increased risk of bleeding, ulcers, and tears (perforation) of the esophagus (tube leading from the mouth to the stomach), stomach and intestines:

○ anytime during use

○ without warning symptoms

○ that may cause death

The risk of getting an ulcer or bleeding increases with:

- past history of stomach ulcers, or stomach or intestinal bleeding with use of NSAIDs
- taking medicines called "corticosteroids", "anticoagulants", "SSRIs", or "SNRIs
- increasing doses of NSAIDs
- longer use of NSAIDs
- smoking
- drinking alcohol
- older age
- poor health
- advanced liver disease
- bleeding problems

NSAIDs should only be used:

- exactly as prescribed
- at the lowest dose possible for your treatment
- for the shortest time needed

What are NSAIDs?

NSAIDs are used to treat pain and redness, swelling, and heat (inflammation) from medical conditions such as different types of arthritis, menstrual cramps, and other types of short-term pain.

Who should not take NSAIDs? Do not take NSAIDs:

- if you have had an asthma attack, hives, or other allergic reaction with aspirin or any other NSAIDs.
- right before or after heart bypass surgery.

Before taking NSAIDS, tell your healthcare provider about all of your medical conditions, including if you:

- have liver or kidney problems
- have high blood pressure
- have asthma
- are pregnant or plan to become pregnant. Talk to your healthcare provivder if you are considering taking NSAIDs during pregnancy. You should not take NSAIDs after 29 weeks of pregnancy.
- are breastfeeding or plan to breast feed .

Tell your healthcare provider about all of the medicines you take, including prescription or over-the- counter medicines, vitamins or herbal supplements. NSAIDs and some other medicines can interact with each other and cause serious side effects. Do not start taking any new medicine without talking to your healthcare provider first.

What are the possible side effects of NSAIDs?

NSAIDs can cause serious side effects, including:

See "What is the most important information I should know about medicines called Nonsteroidal Anti- inflammatory Drugs (NSAIDs)?

- new or worse high blood pressure
- heart failure
- liver problems including liver failure
- kidney problems including kidney failure
- low red blood cells (anemia)
- life-threatening skin reactions
- life threatening allergic reactions
- Other side effects of NSAIDs include: stomach pain, constipation, diarrhea, gas, heartburn, nausea, vomiting, and dizziness.

Get emergency help right away if you get any of the following symptoms:

- shortness of breath or trouble breathing
- chest pain
- weakness in one part or side of your body
- slurred speech
- swelling of the face or throat

Stop taking your NSAID and call your healthcare provider right away if you get any of the following symptoms:

- nausea
- more tired or weaker than usual
- diarrhea
- itching
- your skin or eyes look yellow
- indigestion or stomach pain
- flu-like symptoms
- vomit blood
- there is blood in your bowel movement or it is black and sticky like tar
- unusual weight gain
- skin rash or blisters with fever
- swelling of the arms, legs, hands and feet

If you take too much of your NSAID, call your healthcare provider or get medical help right away.

These are not all the possible side effects of NSAIDs. For more information, ask your healthcare provider or pharmacist about NSAIDs.

Call your doctor for medical advice about side effects. You may report side effects to FDA at 1-800-FDA-1088.

Other information about NSAIDs

- Aspirin is an NSAID but it does not increase the chance of a heart attack. Aspirin can cause bleeding in the brain, stomach, and intestines. Aspirin can also cause ulcers in the stomach and intestines.
- Some NSAIDs are sold in lower doses without a prescription (over-the counter). Talk to your healthcare provider before using over-the-counter NSAIDs for more than 10 days.

General information about the safe and effective use of NSAIDs

Medicines are sometimes prescribed for purposes other than those listed in a Medication Guide. Do not use NSAIDs for a condition for which it was not prescribed. Do not give NSAIDs to other people, even if they have the same symptoms that you have. It may harm them.

If you would like more information about NSAIDs, talk with your healthcare provider. You can ask your pharmacist or healthcare provider for information about NSAIDs that is written for health professionals.

Please address medical inquiries to, (MedicalAffairs@zydususa.com) Tel.: 1-877-993-8779.

This Medication Guide has been approved by the U.S. Food and Drug Administration.

This product's package insert may have been updated. For current package insert, please visit www.zydususa.com

Manufactured by:

Cadila Healthcare Ltd.

Ahmedabad, India

Distributed by:

Zydus Pharmaceuticals USA Inc.

Pennington, NJ 08534

Rev.: 01/16